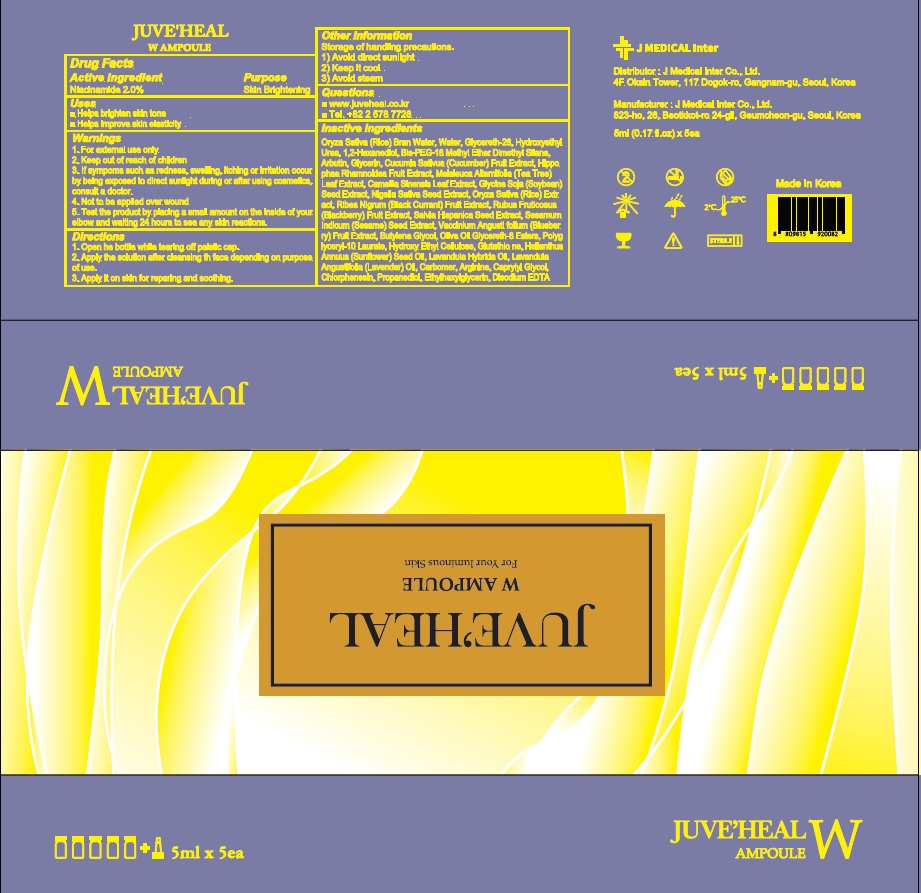 DRUG LABEL: JUVEHEAL W Ampoule
NDC: 81689-030 | Form: LIQUID
Manufacturer: J MEDICAL Inter Co., Ltd.
Category: otc | Type: HUMAN OTC DRUG LABEL
Date: 20210621

ACTIVE INGREDIENTS: Niacinamide 2 g/100 mL
INACTIVE INGREDIENTS: RICE BRAN, DEFATTED; Water; Glycereth-26

ACTIVE INGREDIENT

Niacinamide 2.0%

INACTIVE INGREDIENTS

Oryza Sativa (Rice) Bran Water, Water, Glycereth-26, Hydroxyethyl Urea, 1,2-Hexanediol, Bis-PEG-18 Methyl Ether Dimethyl Silane, Arbutin, Glycerin, Cucumis Sativus (Cucumber) Fruit Extract, Hippophae Rhamnoides Fruit Extract, Melaleuca Alternifolia (Tea Tree) Leaf Extract, Camellia Sinensis Leaf Extract, Glycine Soja (Soybean) Seed Extract, Nigella Sativa Seed Extract, Oryza Sativa (Rice) Extract, Ribes Nigrum (Black Currant) Fruit Extract, Rubus Fruticosus (Blackberry) Fruit Extract, Salvia Hispanica Seed Extract, Sesamum Indicum (Sesame) Seed Extract, Vaccinium Angustifolium (Blueberry) Fruit Extract, Butylene Glycol, Olive Oil Glycereth-8 Esters, Polyglyceryl-10 Laurate, Hydroxy Ethyl Cellulose, Glutathione, Helianthus Annuus (Sunflower) Seed Oil, Lavandula Hybrida Oil, Lavandula Angustifolia (Lavender) Oil, Carbomer, Arginine, Caprylyl Glycol, Chlorphenesin, Propanediol, Ethylhexylglycerin, Disodium EDTA

PURPOSE

Skin Brightening

WARNINGS

1. For external use only
2. Keep out of reach of children
3. If sympoms such as redness, swelling, itching or irritation occur by being exposed to direct sunlight during or after using cosmetics, consult a doctor.
4. Not to be applied over wound
5. Test the product by placing a small amount on the inside of your elbow and waiting 24 hours to see any skin reactions.

KEEP OUT OF REACH OF CHILDREN

Uses

■ Helps brighten skin tone
■ Helps improve skin elasticity

Directions

1. Open he bottle while tearing off palstic cap.
2. Apply the solution after cleansing th face depending on purpose of use.
3. Apply it on skin for reparing and soothing.

Other information

Storage of handling precautions.
1) Avoid direct sunlight
2) Keep it cool
3) Avoid steam

QUESTIONS

■ http://juveheal.co.kr/products.php
■ Tel. +82 2 578 7728